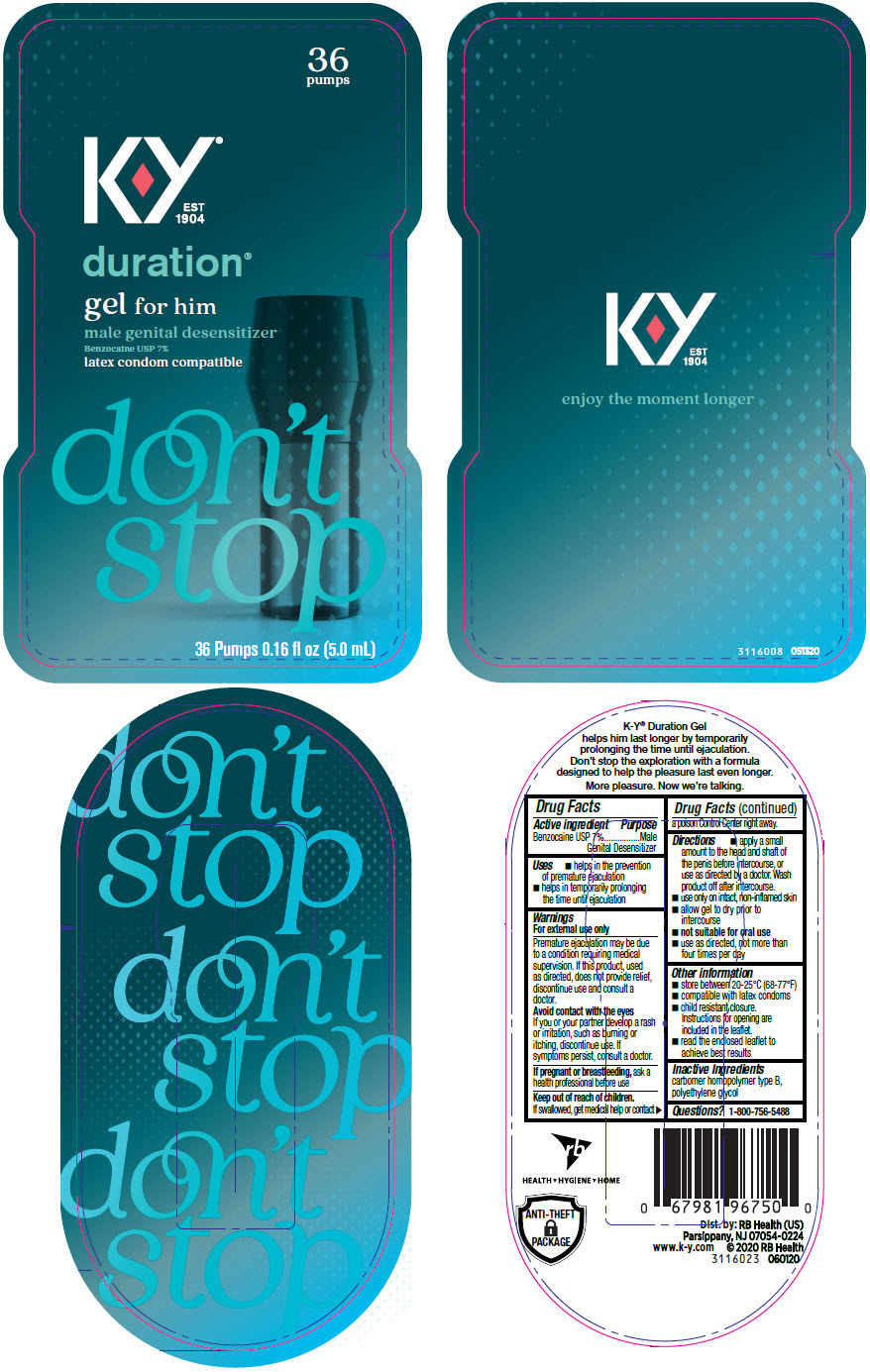 DRUG LABEL: KY Duration for Him
NDC: 72854-683 | Form: GEL
Manufacturer: RB Health (US) LLC
Category: otc | Type: HUMAN OTC DRUG LABEL
Date: 20241223

ACTIVE INGREDIENTS: BENZOCAINE 7 g/100 mL
INACTIVE INGREDIENTS: CARBOMER HOMOPOLYMER TYPE B (ALLYL PENTAERYTHRITOL OR ALLYL SUCROSE CROSSLINKED); POLYETHYLENE GLYCOL, UNSPECIFIED

KY®Duration®Gel for Him

Drug Facts

Active ingredient

Benzocaine USP 7%

Purpose

Male Genital Desensitizer

Uses

- helps in the prevention of premature ejaculation
- helps in temporarily prolonging the time until ejaculation

Warnings

For external use only

Premature ejaculation may be due to a condition requiring medical supervision. If this product, used as directed, does not provide relief, discontinue use and consult a doctor.

Avoid contact with the eyes

If you or your partner develop a rash or irritation, such as burning or itching, discontinue use. If symptoms persist, consult a doctor.

PREGNANCY OR BREAST FEEDING

If pregnant or breastfeeding,ask a health professional before use

Keep out of reach of children.

If swallowed, get medical help or contact a poison Control Center right away.

Directions

- apply a small amount to the head and shaft of the penis before intercourse, or use as directed by a doctor. Wash product off after intercourse.
- use only on intact, non-inflamed skin
- allow gel to dry prior to intercourse
- not suitable for oral use
- use as directed, not more than four times per day

Other information

- store between 20-25°C (68-77°F)
- compatible with latex condoms
- child resistant closure. Instructions for opening are included in the leaflet.
- read the enclosed leaflet to achieve best results

Inactive Ingredients

carbomer homopolymer type B, polyethylene glycol

Questions?

1-800-756-5488

Dist. by:RB Health (US)
Parsippany, NJ 07054-0224

PRINCIPAL DISPLAY PANEL 5.0 mL Can Label

36
pumps

KY®
EST
1904

duration®

gel for him

male genital desensitizer
Benzocaine USP 7%

latex condom compatible

don't
stop

36 Pumps 0.16 fl oz (5.0 mL)